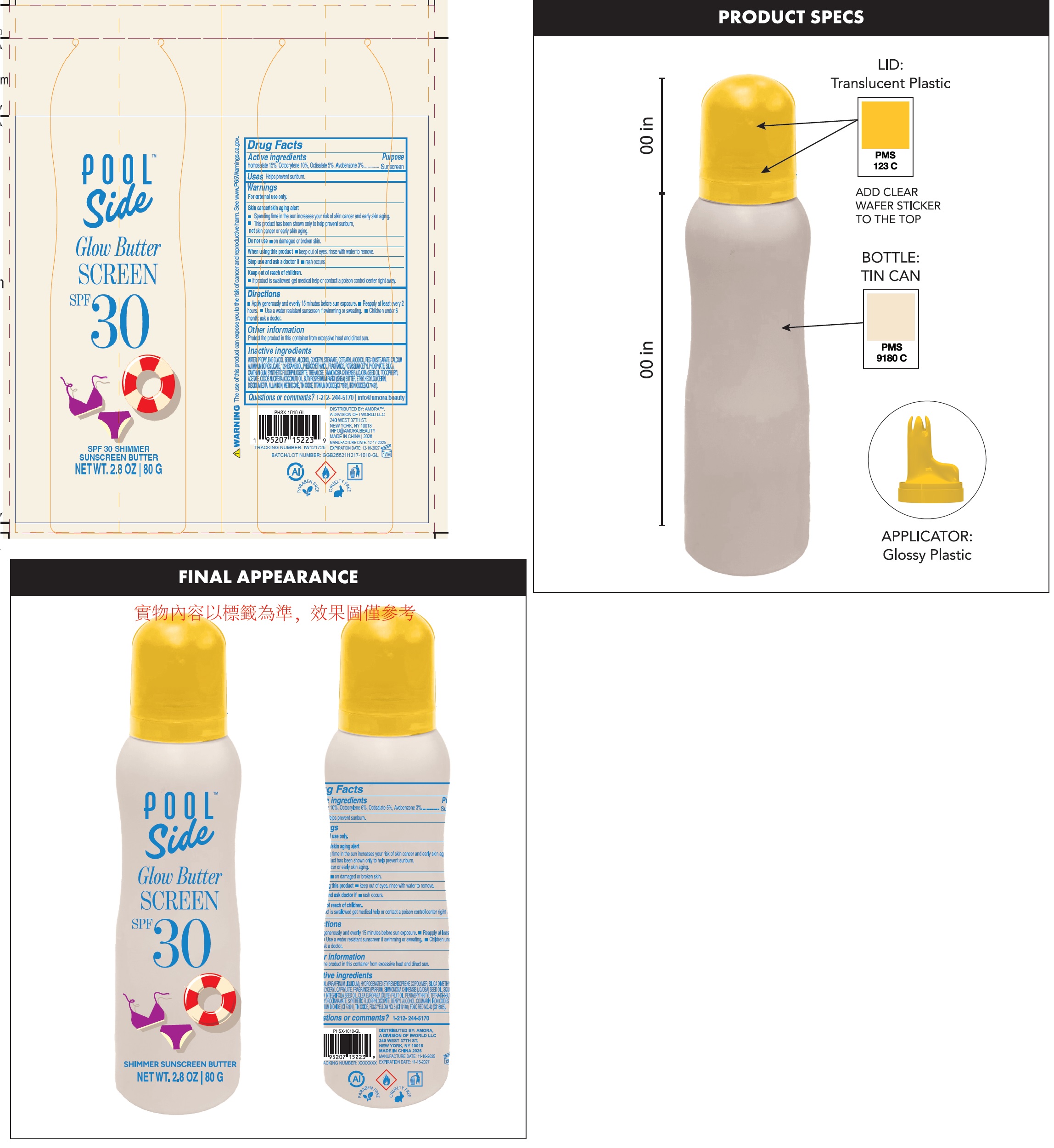 DRUG LABEL: Poolside Glow Butter Screen SPF 30 Shimmer Sunscreen Butter
NDC: 85179-040 | Form: CREAM
Manufacturer: I World LLC
Category: otc | Type: HUMAN OTC DRUG LABEL
Date: 20260210

ACTIVE INGREDIENTS: HOMOSALATE 150 mg/1 g; OCTOCRYLENE 100 mg/1 g; OCTISALATE 50 mg/1 g; AVOBENZONE 30 mg/1 g
INACTIVE INGREDIENTS: WATER; PROPYLENE GLYCOL; BEHENYL ALCOHOL; GLYCERYL MONOSTEARATE; CETOSTEARYL ALCOHOL; PEG-100 MONOSTEARATE; CALCIUM ALUMINUM BOROSILICATE; 1,2-HEXANEDIOL; PHENOXYETHANOL; POTASSIUM CETYL PHOSPHATE; SILICON DIOXIDE; XANTHAN GUM; MAGNESIUM POTASSIUM ALUMINOSILICATE FLUORIDE; TREHALOSE; JOJOBA OIL; .ALPHA.-TOCOPHEROL ACETATE; COCONUT OIL; SHEA BUTTER; ETHYLHEXYLGLYCERIN; EDETATE DISODIUM; ALLANTOIN; STANNIC OXIDE; TITANIUM DIOXIDE; FERRIC OXIDE RED

Poolside Glow Butter Screen SPF 30 Shimmer Sunscreen Butter

Active ingredients

Homosalate 15%, Octocrylene 10%, Octisalate 5%, Avobenzone 3%

Purpose

Sunscreen

Uses

- Helps prevent sunburn.

Warnings

For external use only.
Skin cancer/skin aging alert

- Spending time in the sun increases your risk of skin cancer and early skin aging.
- This product has been shown only to help prevent sunburn, not skin cancer or early skin aging.

Do not use

- on damaged or broken skin.

when using this product

- keep out of eyes. rinse with water to remove.

Stop use and ask a doctor if

- rash occurs.

Keep out of reach of children.

- If product is swallowed get medical help or contact a poison control centre right away.

Directions

- Apply generously and evenly 15 minutes before sun exposer.
- Reapply at least every 2 hours.
- Use a water resistant sunscreen if swimming or sweating.
- Children under 6 month: ask a doctor.

Other information

Protect the product in this container from excessive heat and direct sun.

Inactive ingredients

WATER, PROPYLENE GLYCOL, BEHENYL ALCOHOL, GLYCERYL STEARATE, CETEARYL ALCOHOL, PEG-100 STEARATE, CALCIUM ALUMINUM BOROSILICATE, 1,2-HEXANEDIOL, PHENOXYETHANOL, FRAGRANCE, POTASSIUM CETYL PHOSPHATE, SILICA, XANTHAN GUM, SYNTHETIC FLUORPHLOGOPITE, TREHALOSE, SIMMONDSIA CHINENSIS (JOJOBA) SEED OIL, TOCOPHERYL ACETATE, COCOS NUCIFERA (COCONUT) OIL, BUTYROSPERMUM PARKII (SHEA) BUTTER, ETHYLHEXYLGLYCERIN, DISODIUM EDTA, ALLANTOIN, METHICONE, TIN OXIDE, TITANIUM DIOXIDE(CI 77891), IRON OXIDES(CI 77491).

Questions or comments?

1-212-244-5170 info@amora.beauty